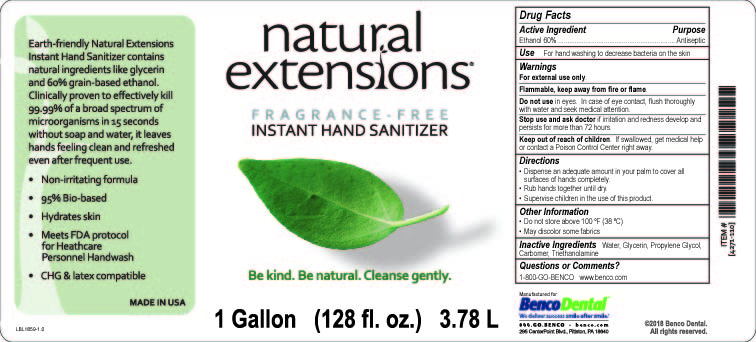 DRUG LABEL: Natural Extensions Fragrance- Free Instant Hand Sanitizer
NDC: 66975-101 | Form: GEL
Manufacturer: Benco Dental
Category: otc | Type: HUMAN OTC DRUG LABEL
Date: 20231128

ACTIVE INGREDIENTS: ALCOHOL 60 mL/100 mL
INACTIVE INGREDIENTS: CARBOMER INTERPOLYMER TYPE A (ALLYL SUCROSE CROSSLINKED); GLYCERIN; PROPYLENE GLYCOL; WATER; TROLAMINE

Natural Extensions Fragrance-Free Instant Hand Sanitizer

Earth-friendly Natural Extensions Instant Hand Sanitizer contains natural ingredients like glycerin and 60% grain-based ethanol. Clinically proven to effectively kill 99.99% of a broad spectrum of microorganisms in 15 seconds without soap and water, it leaves hands feeling clean and refreshed even after frequent use.

- Non-irritating formula
- 95% Bio-based
- Hydrates skin
- Meets FDA protocol for Healthcare Personnel Handwash
- CHG & latex compatible

Active Ingredient

Ethanol 60%

Purpose

Antiseptic

Use

For hand washing to decrease bacteria on the skin

Warnings

For external use only.

Flammable, keep away from fire or flame.

Do not use in eyes. In case of eye contact, flush thoroughly with water and seek medical attention.

Stop use and ask a doctor if irritation and redness develop and persists for more than 72 hours.

Keep out of reach of children. If swallowed get medical help or contact a Poison Control Center right away.

Directions

- Dispense an adequate amount in your palm to cover all surfaces of hands completely.
- Rub hands together until dry.
- Supervise children in the use of this product.

Other Information

- Do not store above 100 ºF (38 ºC)
- May discolor some fabrics

Inactive Ingredients

Water, Glycerin, Propylene Glycol, Carbomer, Triethanolamine

Questions or Comments?

1-800-GO-BENCO www.benco.com